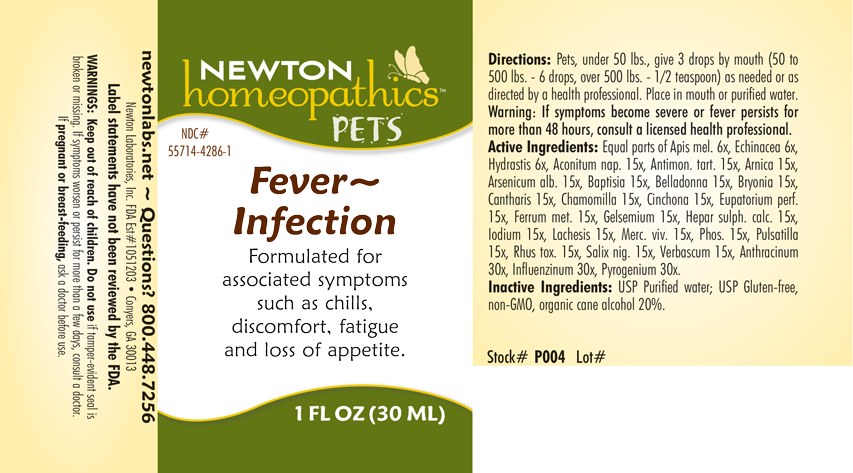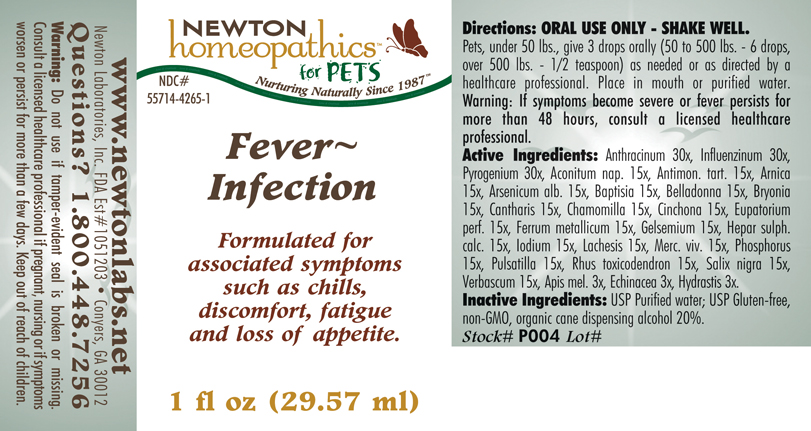 DRUG LABEL: Fever Infection
NDC: 55714-4265 | Form: LIQUID
Manufacturer: Newton Laboratories, Inc.
Category: homeopathic | Type: OTC ANIMAL DRUG LABEL
Date: 20190114

ACTIVE INGREDIENTS: Bacillus Anthracis Immunoserum Rabbit 30 [hp_X]/1 mL; Influenza A Virus 30 [hp_X]/1 mL; Rancid Beef 30 [hp_X]/1 mL; Aconitum Napellus 15 [hp_X]/1 mL; Antimony Potassium Tartrate 15 [hp_X]/1 mL; Arnica Montana 15 [hp_X]/1 mL; Arsenic Trioxide 15 [hp_X]/1 mL; Baptisia Tinctoria Root 15 [hp_X]/1 mL; Atropa Belladonna 15 [hp_X]/1 mL; Bryonia Alba Root 15 [hp_X]/1 mL; Lytta Vesicatoria 15 [hp_X]/1 mL; Matricaria Recutita 15 [hp_X]/1 mL; Cinchona Officinalis Bark 15 [hp_X]/1 mL; Eupatorium Perfoliatum Flowering Top 15 [hp_X]/1 mL; Iron 15 [hp_X]/1 mL; Gelsemium Sempervirens Root 15 [hp_X]/1 mL; Calcium Sulfide 15 [hp_X]/1 mL; Iodine 15 [hp_X]/1 mL; Lachesis Muta Venom 15 [hp_X]/1 mL; Mercury 15 [hp_X]/1 mL; Phosphorus 15 [hp_X]/1 mL; Pulsatilla Vulgaris 15 [hp_X]/1 mL; Toxicodendron Pubescens Leaf 15 [hp_X]/1 mL; Salix Nigra Bark 15 [hp_X]/1 mL; Verbascum Thapsus 15 [hp_X]/1 mL; Apis Mellifera 3 [hp_X]/1 mL; Echinacea, Unspecified 3 [hp_X]/1 mL; Goldenseal 3 [hp_X]/1 mL; Influenza B Virus 30 [hp_X]/1 mL
INACTIVE INGREDIENTS: Alcohol

Fever - Infection

PRODUCT NAME & INDICATIONS SECTION

Fever~Infection Formulated for associated symptoms such as chills, discomfort, fatigue and loss of appetite.

DIRECTIONS SECTION

Directions: Pets, under 50 lbs., give 3 drops by mouth (50 to 500 lbs. - 6 drops, over 500 lbs. - 1/2 teaspoon) as needed or as directed by a health professional. Place in mouth or purified water. Warning: If symptoms become severe or fever persists for more than 48 hours, consult a licensed health professional.

ACTIVE INGREDIENT SECTION

Equal parts of Apis mel. 6x, Echinacea 6x, Hydrastis 6x, Aconitum nap.15x, Antimon. tart.15x, Arnica 15x, Arsenicum alb.15x, Baptisia 15x, Belladonna 15x, Bryonia 15x, Cantharis 15x, Chamomilla 15x, Cinchona 15x, Eupatorium perf.15x, Ferrum metallicum 15x, Gelsemium 15x, Hepar sulph. calc.15x, Iodium 15x, Lachesis 15x, Merc. viv.15x, Phosphorus 15x, Pulsatilla 15x, Rhus toxicodendron 15x, Salix nigra 15x, Verbascum 15x, Anthracinum 30x, Influenzinum 30x, Pyrogenium 30x .

INACTIVE INGREDIENT SECTION

Inactive Ingredients: USP Purified water; USP Gluten-free, non-GMO, organic cane alcohol 20%.

QUESTIONS? SECTION

netwonlabs.net Questions? 1.800.448.7256
Newton Laboratories, Inc. FDA Est # 1051203 - Conyers, GA 30013

WARNINGS SECTION

WARNINGS: Keep out of reach of children. Do not use if tamper-evident seal is broken or missing. If symptoms worsen or persist for more than a few days, consult a doctor. If pregnant or breast-feeding, ask a doctor before use.

OTC - PREGNANCY OR BREAST FEEDING SECTION

If pregnant or breast-feeding, ask a doctor before use.

OTC - KEEP OUT OF REACH OF CHILDREN SECTION

Keep out of reach of children.